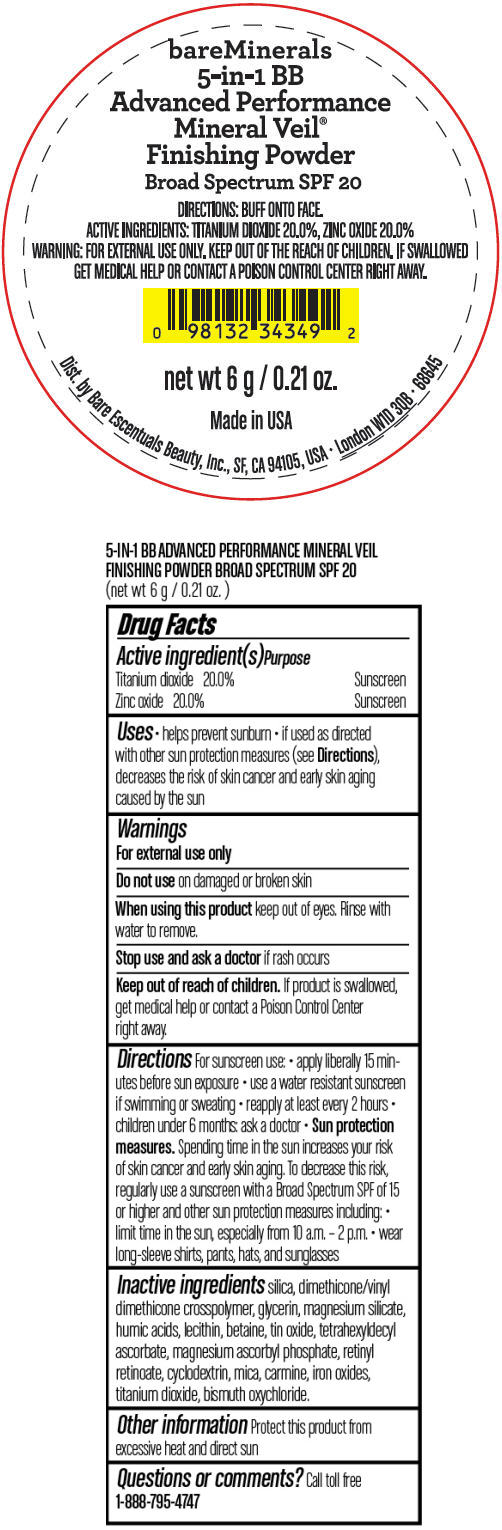 DRUG LABEL: bareMinerals 5-in-1 BB Advanced Performance Mineral Veil Finishing Broad Spectrum SPF 20
NDC: 98132-750 | Form: POWDER
Manufacturer: Bare Escentuals Beauty, Inc.
Category: otc | Type: HUMAN OTC DRUG LABEL
Date: 20140318

ACTIVE INGREDIENTS: Titanium Dioxide 0.2 g/1 g; Zinc Oxide 0.2 g/1 g
INACTIVE INGREDIENTS: SILICON DIOXIDE; GLYCERIN; MAGNESIUM SILICATE; BETAINE; STANNIC OXIDE; TETRAHEXYLDECYL ASCORBATE; MAGNESIUM ASCORBYL PHOSPHATE; RETINYL RETINOATE; MICA; FERRIC OXIDE RED; BISMUTH OXYCHLORIDE

5-IN-1 BB ADVANCED PERFORMANCE
MINERAL VEIL FINISHING POWDER BROAD SPECTRUM SPF 20
(net wt 6 g / 0.21 oz.)

Drug Facts

ACTIVE INGREDIENT

Active ingredient(s) | Purpose
Titanium dioxide 20.0% | Sunscreen
Zinc oxide 20.0% | Sunscreen

Uses

- helps prevent sunburn
- if used as directed with other sun protection measures (see Directions), decreases the risk of skin cancer and early skin aging caused by the sun

Warnings

For external use only

Do not use on damaged or broken skin

When using this product keep out of eyes. Rinse with water to remove.

Stop use and ask a doctor if rash occurs

Keep out of reach of children. If product is swallowed, get medical help or contact a Poison Control Center right away.

Directions

For sunscreen use:

- apply liberally 15 minutes before sun exposure
- use a water resistant sunscreen if swimming or sweating
- reapply at least every 2 hours
- children under 6 months: ask a doctor
- Sun protection measures. Spending time in the sun increases your risk of skin cancer and early skin aging. To decrease this risk, regularly use a sunscreen with a Broad Spectrum SPF of 15 or higher and other sun protection measures including:
  - limit time in the sun, especially from 10 a.m. – 2 p.m.
  - wear long-sleeve shirts, pants, hats, and sunglasses

Inactive ingredients

silica, dimethicone/vinyl dimethicone crosspolymer, glycerin, magnesium silicate, humic acids, lecithin, betaine, tin oxide, tetrahexyldecyl ascorbate, magnesium ascorbyl phosphate, retinyl retinoate, cyclodextrin, mica, carmine, iron oxides, titanium dioxide, bismuth oxychloride.

Other information

Protect this product from excessive heat and direct sun

Questions or comments?

Call toll free 1-888-795-4747

PRINCIPAL DISPLAY PANEL - 6 g Jar Label

bareMinerals
5-in-1 BB
Advanced Performance
Mineral Veil®
Finishing Powder
Broad Spectrum SPF 20

DIRECTIONS: BUFF ONTO FACE.
ACTIVE INGREDIENTS: TITANIUM DIOXIDE 20.0%, ZINC OXIDE 20.0%
WARNING: FOR EXTERNAL USE ONLY. KEEP OUT OF THE REACH OF CHILDREN. IF SWALLOWED
GET MEDICAL HELP OR CONTACT A POISON CONTROL CENTER RIGHT AWAY.

net wt 6 g / 0.21 oz.

Made in USA

Dist. by Bare Escentuals Beauty, Inc., SF, CA 94105, USA • London W1D 3QB • 68645